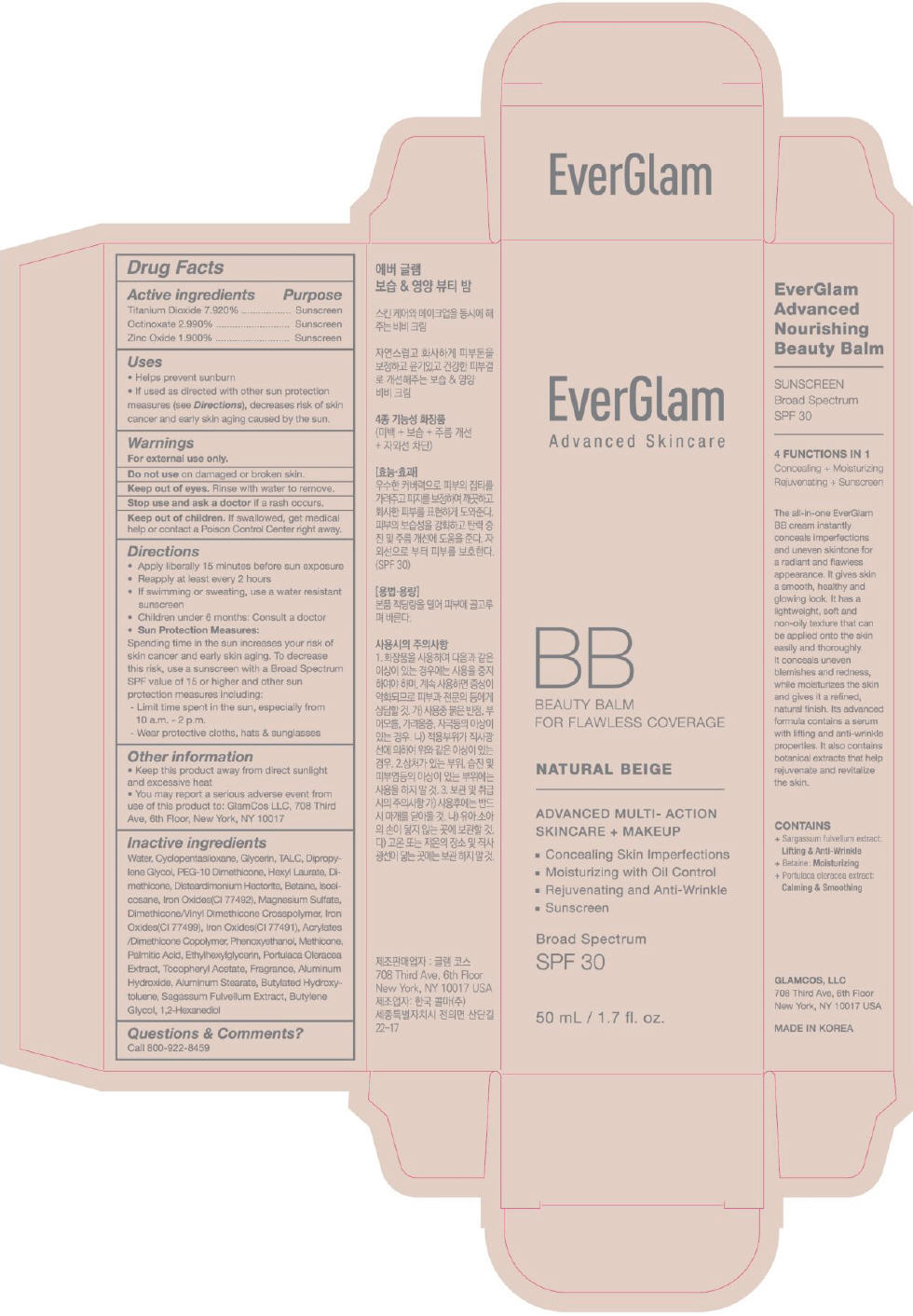 DRUG LABEL: EverGlam BB Natural Beige
NDC: 71667-200 | Form: CREAM
Manufacturer: Glamcos L.L.C.
Category: otc | Type: HUMAN OTC DRUG LABEL
Date: 20170828

ACTIVE INGREDIENTS: TITANIUM DIOXIDE 79.2 mg/1 mL; Octinoxate 29.9 mg/1 mL; ZINC OXIDE 19 mg/1 mL
INACTIVE INGREDIENTS: Water; CYCLOMETHICONE 5; Glycerin; Talc; Dipropylene Glycol; PEG-10 DIMETHICONE (600 CST); Hexyl Laurate; Dimethicone; Disteardimonium Hectorite; Betaine; Isoeicosane; FERRIC OXIDE RED; FERRIC OXIDE YELLOW; FERROSOFERRIC OXIDE; Magnesium Sulfate, Unspecified Form; DIMETHICONE/VINYL DIMETHICONE CROSSPOLYMER (SOFT PARTICLE); Phenoxyethanol; Methicone (20 Cst); Palmitic Acid; Ethylhexylglycerin; PURSLANE; .ALPHA.-TOCOPHEROL ACETATE; Aluminum Hydroxide; ALUMINUM MONOSTEARATE; BUTYLATED HYDROXYTOLUENE; Sargassum Fulvellum; Butylene Glycol; 1,2-Hexanediol

EverGlam BB Cream Natural Beige

Drug Facts

ACTIVE INGREDIENT

Active Ingredients | Purpose
Titanium Dioxide 7.920% | Sunscreen
Octinoxate 2.99% | Sunscreen
Zinc Oxide 1.900% | Sunscreen

Uses

- Helps prevent sunburn
- If used as directed with other sun protection measures (see Directions), decreases risk of skin cancer and early skin aging caused by the sun.

Warnings

For external use only.

Do not use on damaged or broken skin.

WHEN USING

Keep out of eyes. Rinse with water to remove.

Stop use and ask a doctor if a rash occurs.

KEEP OUT OF REACH OF CHILDREN

Keep out of children. If swallowed, get medical help or contact a Poison Control Center right away.

Directions

- Apply liberally 15 minutes before sun exposure
- Reapply at least every 2 hours
- If swimming or sweating, use a water resistant sunscreen
- Children under 6 months: Consult a doctor
- Sun Protection Measures:
  Spending time in the sun increases your risk of skin cancer and early skin aging. To decrease this risk, use a sunscreen with a Broad Spectrum SPF value of 15 or higher and other sun protection measures including:
  - Limit time spent in the sun, especially from 10 a.m. - 2p.m.
  - Wear protective cloths, hats & sunglasses

Other information

- Keep this product away from direct sunlight and excessive heat
- You may report a serious adverse event from use of this product to: GlamCos LLC, 708 Third Ave, 6th Floor, New York, NY 10017

Inactive ingredients

Water, Cyclopentasiloxane, Glycerin, TALC, Dipropylene Glycol, PEG-10 Dimethicone, Hexyl Laurate, Dimethicone, Disteardimonium Hectorite, Betaine, Isoeicosane, Iron Oxides(CI 77492), Magnesium Sulfate, Dimethicone/Vinyl Dimethicone Crosspolymer, Iron Oxides(CI 77499), Iron Oxides(CI 77491), Acrylates/Dimethicone Copolymer, Phenoxyethanol, Methicone, Palmitic Acid, Ethylhexylglycerin, Portulaca Oleracea Extract, Tocopheryl Acetate, Fragrance, Aluminum Hydroxide, Aluminum Stearate, Butylated Hydroxytoluene, Sagassum Fulvellum Extract, Butylene Glycol, 1,2-Hexanediol

Questions & Comments?

Call 800-922-8459

PRINCIPAL DISPLAY PANEL - 50 mL Tube Box

EverGlam
Advanced Skincare

BB
BEAUTY BALM
FOR FLAWLESS COVERAGE

NATURAL BEIGE

ADVANCED MULTI- ACTION
SKINCARE + MAKEUP

- Concealing Skin Imperfections
- Moisturizing with Oil Control
- Rejuvenating and Anti-Wrinkle
- Sunscreen

Broad Spectrum
SPF 30

50 mL / 1.7 fl. oz.